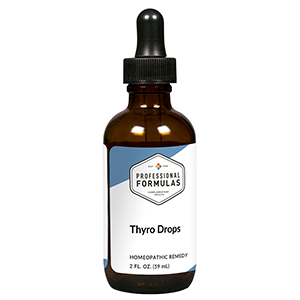 DRUG LABEL: Thyro Drops
NDC: 63083-5028 | Form: LIQUID
Manufacturer: Professional Complementary Health Formulas
Category: homeopathic | Type: HUMAN OTC DRUG LABEL
Date: 20190815

ACTIVE INGREDIENTS: SPONGIA OFFICINALIS SKELETON, ROASTED 3 [hp_X]/59 mL; CALCIUM IODIDE 4 [hp_X]/59 mL; SUS SCROFA ADRENAL GLAND 6 [hp_X]/59 mL; FUCUS VESICULOSUS 6 [hp_X]/59 mL; POTASSIUM IODIDE 6 [hp_X]/59 mL; CALCIUM HEXAFLUOROSILICATE 6 [hp_X]/59 mL; BOS TAURUS PITUITARY GLAND, POSTERIOR 6 [hp_X]/59 mL; BOS TAURUS SPLEEN 6 [hp_X]/59 mL; HYSSOPUS OFFICINALIS WHOLE 6 [hp_X]/59 mL; THYROID, UNSPECIFIED 6 [hp_X]/59 mL; OYSTER SHELL CALCIUM CARBONATE, CRUDE 8 [hp_X]/59 mL; FERROUS IODIDE 8 [hp_X]/59 mL; CALCIUM SULFIDE 8 [hp_X]/59 mL; IODINE 9 [hp_X]/59 mL
INACTIVE INGREDIENTS: ALCOHOL; WATER

HTD

ACTIVE INGREDIENTS

Spongia tosta 3X
Calcarea iodata 4X
Adrenal 6X
Fucus vesiculosus 6X
Kali iodatum 6X
Lapis albus 6X
Pituitary 6X
Spleen 6X
Thymus 6X
Thyroid 6X
Calcarea carbonica 8X
Ferrum iodatum 8X
Hepar sulphuris calcareum 8X
Iodium 9X

QUESTIONS

Professional Formulas

PO Box 2034 Lake Oswego, OR 97035

INDICATIONS

For the temporary relief of cough, shortness of breath, weight gain, dry skin, constipation, or fatigue.*

PURPOSE

*Claims based on traditional homeopathic practice, not accepted medical evidence. Not FDA evaluated.

WARNINGS

In case of overdose, get medical help or contact a poison control center right away.

Keep out of the reach of children.

PREGNANCY OR BREAST FEEDING

If pregnant or breastfeeding, ask a healthcare professional before use.

DIRECTIONS

Place drops under tongue 30 minutes before/after meals. Adults and children 12 years and over: Take 10 drops up to 3 times per day. Consult a physician for use in children under 12 years of age.

OTHER INFORMATION

Tamper resistant. If seal is broken, do not use. After opening, close container tightly and store at room temperature away from heat.

INACTIVE INGREDIENTS

20% ethanol, purified water.

LABEL

Est 1985

Professional Formulas

Complementary Health

Thyro Drops

Homeopathic Remedy

2 FL. OZ. (59 mL)